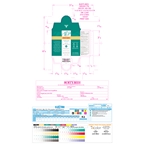 DRUG LABEL: NAS Targeted Spot Treatment
NDC: 26052-041 | Form: LIQUID
Manufacturer: Burt's Bees
Category: otc | Type: HUMAN OTC DRUG LABEL
Date: 20231005

ACTIVE INGREDIENTS: SALICYLIC ACID 0.75 g/100 g
INACTIVE INGREDIENTS: GLYCERIN; CENTELLA ASIATICA LEAF; CALENDULA OFFICINALIS FLOWER; FENNEL OIL; EUCALYPTUS GLOBULUS LEAF; LEMON OIL; BORAGO OFFICINALIS SEED; PARSLEY OIL; SALIX NIGRA BARK; TEA TREE OIL; JUNIPER BERRY OIL; ACHILLEA MILLEFOLIUM; ALCOHOL; WATER

Natural Acne Solutions Targeted Spot Treatment with Cica 284874.001

ACTIVE INGREDIENT

Salicylic Acid 0.75%

PURPOSE

Acne Treatment

Uses

- For the treatment of acne. Clears

acne blemishes, acne pimples, blackheads,
and whiteheads

Warnings

For external use only. Skin irritation and dryness is more likely to occur if
you use another topical acne medication at the
same time. If irritation occurs, only one medication
should be used unless directed by a doctor.

Keep out of reach of children.

If swallowed, get medical help or contact a Poison Control Center right away.

Keep Out of Reach of Children

If swallowed, get medical help or contact a Poison Control Center right away.

Directions

• Clean the skin thoroughly before applying the product, Cover the blemish with a thin layer one to three times a day • Avoid
the eye area, if contact occurs rinse thoroughly with water • Because excessive dryness may occur, start with one application daily, then increase to two or three times daily if needed or as directed by a doctor • If bothersome dryness or peeling occurs, reduce application to once a day or every other day

INACTIVE INGREDIENT

Inactive Ingredients: alcohol denat., citrus limon (lemon) peel oil, water,achillea millefolium extract, borago officinalis extract, calendula officinalis flower extract, carum petroselinum (parsley) extract, foeniculum vulgare (fennel) oil, salix nigra (willow) bark extract, glycerin, melaleuca alternifolia (tea tree) leaf oil, centella asiatica leaf extract, eucalyptus globulus leaf oil, juniperus communis fruit oil

Questions? 800-849-7112 or www.burtsbees.com

PACKAGE LABEL

BURT'S BEES

NATURAL ACNE

SOLUTIONS

Targeted

Spot Treatment

salicylic acid acne treatment

with soothing cica

Instantly starts working to

penetrate & clear clogged pores

99.9% Natural Origin

0.26 fl oz / 7.68 ml